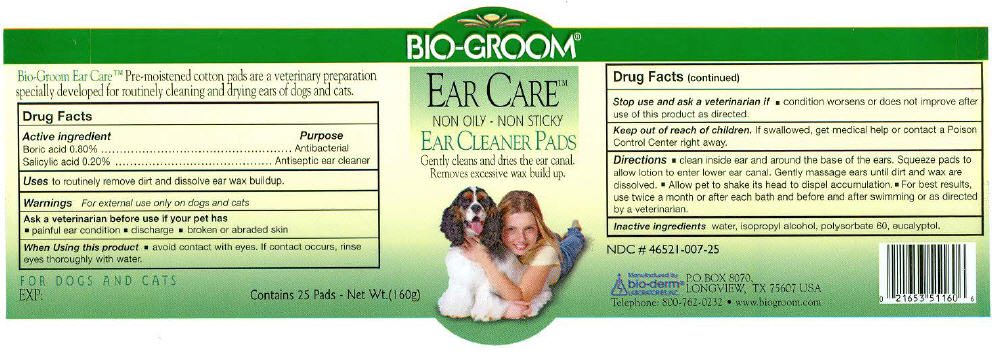 DRUG LABEL: Bio-Groom 
NDC: 46521-007 | Form: SOLUTION
Manufacturer: Bio-Derm Laboratories Inc.
Category: animal | Type: OTC ANIMAL DRUG LABEL
Date: 20110713

ACTIVE INGREDIENTS: BORIC ACID 0.8 mg/1 1; SALICYLIC ACID 0.2 mg/1 1
INACTIVE INGREDIENTS: WATER; ISOPROPYL ALCOHOL; POLYSORBATE 60; EUCALYPTOL

Bio-Groom
Ear-Care
Ear Cleaner Pads

ACTIVE INGREDIENT

Active Ingredient | Purpose
Boric acid 0.8% | Antibacterial
Salicylic acid 0.20% | Antiseptic ear cleaner

Uses

to routinely remove dirt and dissolve ear wax buildup

Warnings

For external use only on dogs and cats

Ask a veterinarian before use if your pet has

- painful ear condition
- discharge
- broken or abraded skin

When using this product

- avoid contact with eyes. If contact occurs rinse eyes thoroughly with water.

Stop use and ask a veterinarian if

- condition worsens or does not improve after use of this product as directed.

Keep out of reach of children. If swallowed, get medical help or contact a Poison Control Center right away.

Directions

- Thoroughly clean inside ear and around the base of the ears. Squeeze Ear Care Pads to allow lotion to enter lower ear canal. Gently massage ears until dirt and wax are dissolved.
- Allow pet to shake its head to dispel accumulation.
- For best results, use twice a month or after each bath and before and after swimming or as directed by a veterinarian.

Inactive ingredients

water, isopropyl alcohol, polysorbate 60, eucalyptol

Manufactured by
bio-derm®
LABORATORIES,INC.
P.O. Box 8070,
LONGVIEW, TX 75607 USA

PRINCIPAL DISPLAY PANEL - 160g Bottle Label

BIO-GROOM®

EAR CARE™

NON OILY - NON STICKY

EAR CLEANER PADS

Gently cleans and dries the ear canal.
Removes excessive wax build up.